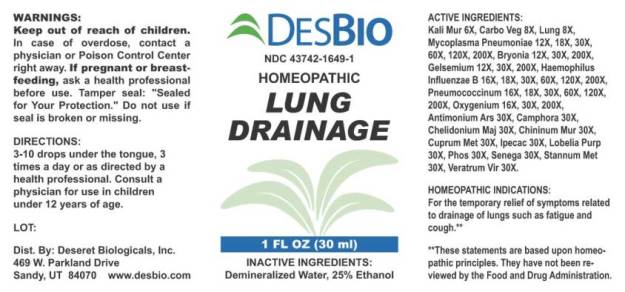 DRUG LABEL: Lung Drainage
NDC: 43742-1649 | Form: LIQUID
Manufacturer: Deseret Biologicals, Inc.
Category: homeopathic | Type: HUMAN OTC DRUG LABEL
Date: 20240115

ACTIVE INGREDIENTS: POTASSIUM CHLORIDE 6 [hp_X]/1 mL; ACTIVATED CHARCOAL 8 [hp_X]/1 mL; SUS SCROFA LUNG 8 [hp_X]/1 mL; MYCOPLASMA PNEUMONIAE 12 [hp_X]/1 mL; BRYONIA ALBA ROOT 12 [hp_X]/1 mL; GELSEMIUM SEMPERVIRENS ROOT 12 [hp_X]/1 mL; HAEMOPHILUS INFLUENZAE TYPE B 16 [hp_X]/1 mL; STREPTOCOCCUS PNEUMONIAE 16 [hp_X]/1 mL; OXYGEN 16 [hp_X]/1 mL; ANTIMONY ARSENATE 30 [hp_X]/1 mL; CAMPHOR (NATURAL) 30 [hp_X]/1 mL; CHELIDONIUM MAJUS WHOLE 30 [hp_X]/1 mL; QUININE HYDROCHLORIDE 30 [hp_X]/1 mL; COPPER 30 [hp_X]/1 mL; IPECAC 30 [hp_X]/1 mL; PRATIA PURPURASCENS 30 [hp_X]/1 mL; PHOSPHORUS 30 [hp_X]/1 mL; POLYGALA SENEGA ROOT 30 [hp_X]/1 mL; TIN 30 [hp_X]/1 mL; VERATRUM VIRIDE ROOT 30 [hp_X]/1 mL
INACTIVE INGREDIENTS: WATER; ALCOHOL

Drug Facts:

ACTIVE INGREDIENTS:

Kali Muriaticum 6X, Carbo Vegetabilis 8X, Lung (Suis) 8X, Mycoplasma Pneumoniae 12X, 18X, 30X, 60X, 120X, 200X, Bryonia (Alba) 12X, 30X, 200X, Gelsemium Sempervirens 12X, 30X, 200X, Haemophilus Influenzae B 16X, 18X, 30X, 60X, 120X, 200X, Pneumococcinum 16X, 18X, 30X, 60X, 120X, 200X, Oxygenium 16X, 30X, 200X, Antimonium Arsenicicum 30X, Camphora 30X, Chelidonium Majus 30X, Chininum Muriaticum 30X, Cuprum Metallicum 30X, Ipecacuanha 30X, Lobelia Purpurescens 30X, Phosphorus 30X, Senega Officinalis 30X, Stannum Metallicum 30X, Veratrum Viride 30X.

HOMEOPATHIC INDICATIONS:

For temporary relief of symptoms related to drainage of lungs such as fatigue and cough.**

**These statements are based upon homeopathic principles. They have not been reviewed by the Food and Drug Administration.

WARNINGS:

Keep out of reach of children. In case of overdose, contact a physician or Poison Control Center right away.

If pregnant or breast-feeding, ask a health professional before use.

Tamper seal: "Sealed for Your Protection." Do not use if seal is broken or missing.

Keep out of reach of children. In case of overdose, contact a physician or Poison Control Center right away.

DIRECTIONS:

3-10 drops under the tongue, 3 times a day or as directed by a health professional. Consult a physician for use in children uner 12 years of age.

HOMEOPATHIC INDICATIONS:

For temporary relief of symptoms related to drainage of lungs such as fatigue and cough.**

**These statements are based upon homeopathic principles. They have not been reviewed by the Food and Drug Administration.

INACTIVE INGREDIENTS:

Demineralized Water, 25% Ethanol

QUESTIONS:

Dist. By: Deseret Biologicals, Inc.
469 W. Parkland Drive
Sandy, UT 84070 www.desbio.com

PACKAGE LABEL DISPLAY:

DESBIO
NDC 43742-1649-1
HOMEOPATHIC
LUNG

DRAINAGE

1 FL OZ (30 ml)